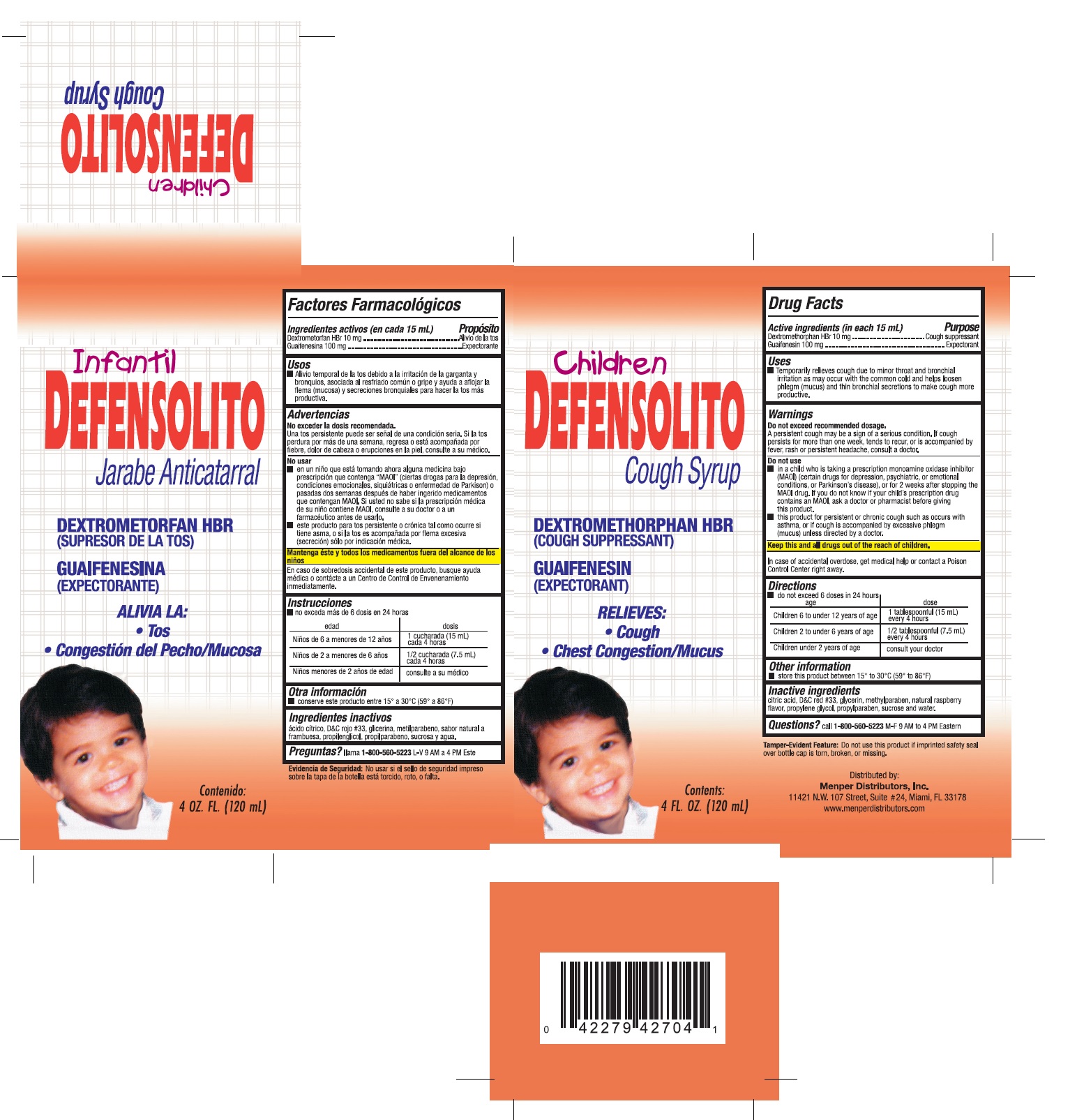 DRUG LABEL: Defensolito Children Syrup
NDC: 53145-008 | Form: LIQUID
Manufacturer: Menper Distributors, Inc.
Category: otc | Type: HUMAN OTC DRUG LABEL
Date: 20220218

ACTIVE INGREDIENTS: GUAIFENESIN 100 mg/15 mL; DEXTROMETHORPHAN HYDROBROMIDE 10 mg/15 mL
INACTIVE INGREDIENTS: CITRIC ACID ACETATE; D&C RED NO. 33; GLYCERIN; METHYLPARABEN; RASPBERRY; PROPYLENE GLYCOL; PROPYLPARABEN; WATER; SUCROSE

Active ingredients (in each 15mL tsp)

Guaifenesin 100 mg………………………………Expectorant

Dextromethorphan HBr 10 mg……………………Cough suppressant

Purpose

Expectorant

Cough Suppressant

Uses

Temporarily relieves cough due to minor throat and bronchial irritation and nasal congestion as may occur with the common cold and help loosen phlegm (mucus) and thin bronchial secretions to make cough more productive.

Warnings Do not exceed recommended dosage.

A persistent cough may be a sign of a serious condition. If cough oersistent for more than one week, tends to recur, or is accompanied by fever, rash or persistent headache, consult a doctor.

Do not use:

- in a child who is taking a prescription monoamine oxidase inhibitor (MAOI)(certain drugs for depression, psychiatric, or emotional conditions, or parkinson's disease), or for 2 weeks after stopping the MAOI drug. If you do not know if your child's prescription drug contains an MAOI ask a doctor or a pharmacist giving this product.
- this product for persistent or chronic cough such as occur with asthma, or if cough is accompanied ny excessive phlegm (mucus) unless directed by a doctor.

Keep this and all drugs out of the reach of children

In case of accidental overdose, get medical help or contact a Poison Control Center right away.

Directions

do not exceed 6 doses in 24 hours

Age | Dose
Children 6 to under 12 years of age | 1 tablespoonful (15mL) every 4 hours
Children 2 to under 6 years of age | 1/2 tablespoonful (7.5 mL) every 4 hours
Children under 2 years of age | consult your doctor

Other information

store this product between 15° to 30° C (59° to 86°F)

Inactive ingredients

citric acid, D&C red #33, glycerin, methylparaben, natural raspberry flavor, propylene glycol, propylparaben, sucrose and water.

Question?

call 1-800-560-5223 M-F 9 AM to 4 PM Eastern